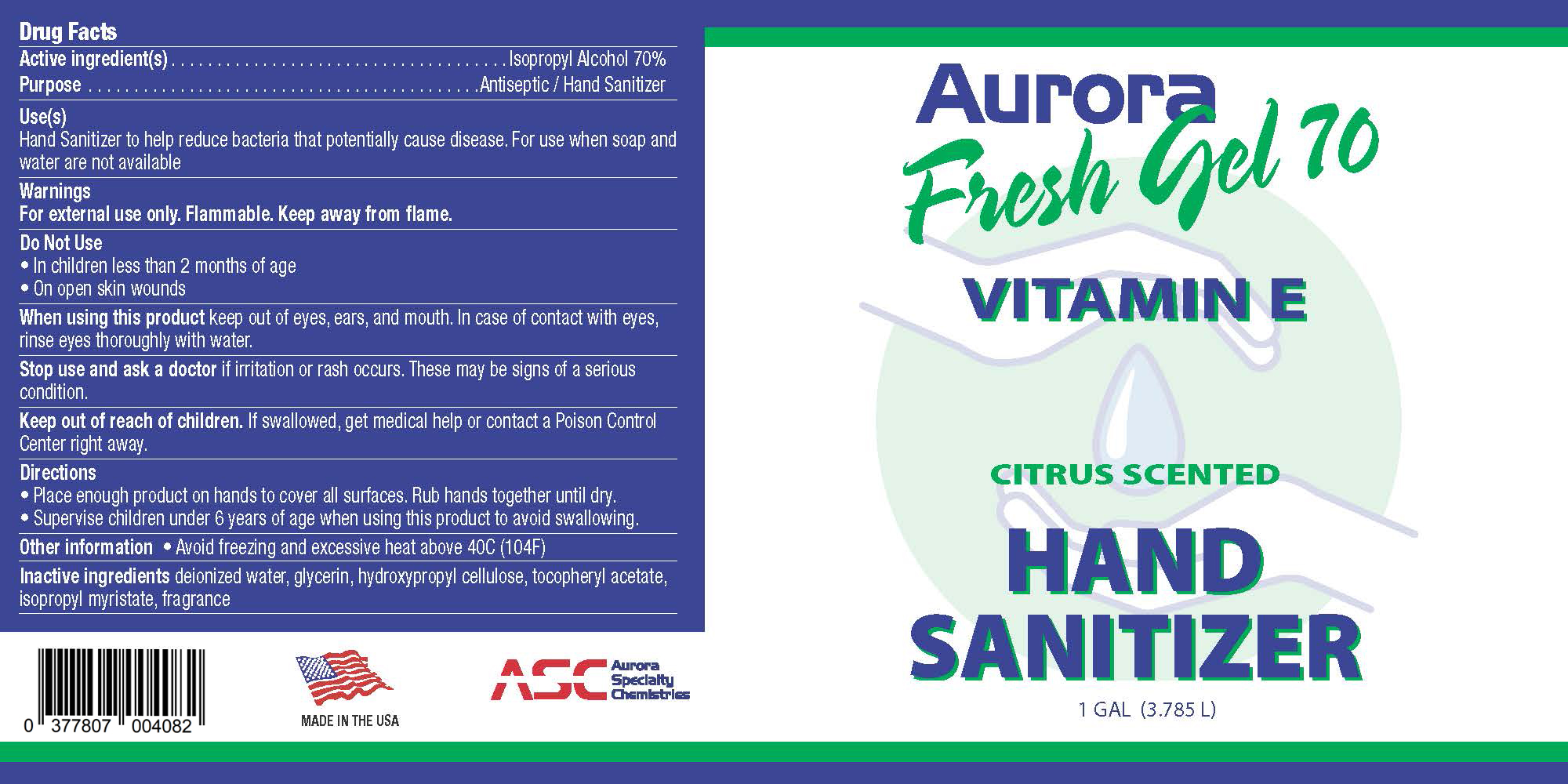 DRUG LABEL: Aurora Fresh Gel 70
NDC: 77807-004 | Form: GEL
Manufacturer: Aurora Specialty Chemistries
Category: otc | Type: HUMAN OTC DRUG LABEL
Date: 20220128

ACTIVE INGREDIENTS: ISOPROPYL ALCOHOL 70 L/1 L
INACTIVE INGREDIENTS: WATER 27.7 L/1 L; HYDROXYPROPYL CELLULOSE (1600000 WAMW) 0.7 L/1 L; GLYCERIN 1.39 L/1 L; ISOPROPYL MYRISTATE 0.07 L/1 L; .ALPHA.-TOCOPHEROL ACETATE, DL- 0.07 L/1 L; CITRAL 0.07 L/1 L

Aurora Fresh Gel 70 Citrus Scented Gel Hand Sanitizer with Vitamin E 1 Gallon (3.785L) Container with Hand Pump

This is a gel hand sanitizer with citrus fragrance manufactured according to standard CGMP.
The hand sanitizer is manufactured using only the following United States Pharmacopoeia (USP) grade ingredients in the preparation of the product (percentage in final product formulation) consistent with existing hand sanitizer products sold OTC throughout the United States and Globally:

Isopropyl Alcohol (70%, v/v) in an aqueous solution denatured according to Alcohol and Tobacco Tax and Trade Bureau regulations in 27 CFR part 20.
Glycerin (1.39% v/v).
Hydroxymethyl Cellulose (0.7% v/v).
Isopropyl Myristate (0.07% v/v)
DL-Alpha-Tocopherol Acetate (0.07% v/v)
Citral (0.07% v/v)
Sterile distilled water (27.7% v/v).

The firm does not add other active or inactive ingredients. Different or additional ingredients may impact the quality and potency of the product.

Active Ingredient(s)

Isopropyl Alcohol 70%

Purpose

Antiseptic / Hand Sanitizer

Use(s)

Hand Sanitizer to help reduce bacteria that potentially cause disease.
For use when soap and water are not available.

Warnings

For external use only. Flammable. Keep away from flame.

Do Not Use

- In children less than 2 months of age
- On open skin wounds

When using this product keep out of eyes, ears, and mouth. In case of contact with eyes, rinse eyes thoroughly with water.

Stop use and ask a doctor if irritation or rash occurs. These may besigns of a serious condition.

Keep out of reach of children. If swallowed, get medical help or contact a Poison Control Center right away.

Stop use and ask a doctor if irritation or rash occurs. These may besigns of a serious condition.

Keep out of reach of children. If swallowed, get medical help or contact a Poison Control Center right away.

Directions

• Place enough product on hands to cover all surfaces. Rub hands together until dry.
• Supervise children under 6 years of age when using this product to avoid swallowing.

Other Information

Avoid freezing and excessive heat above 40C (104F)

Inactive ingredients

deionized water, glycerin, hydroxypropyl cellulose, tocopheryl acetate, isopropyl myristate, fragrance

Package Label - Principal Display Panel

1 Gallon (3.785 L) NDC: 77807-004-08